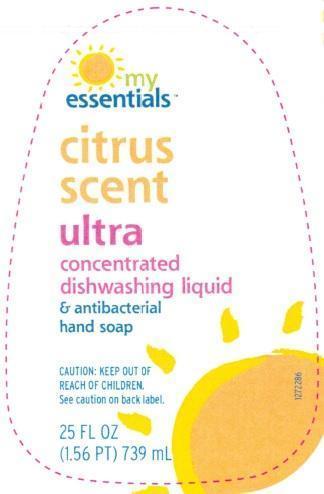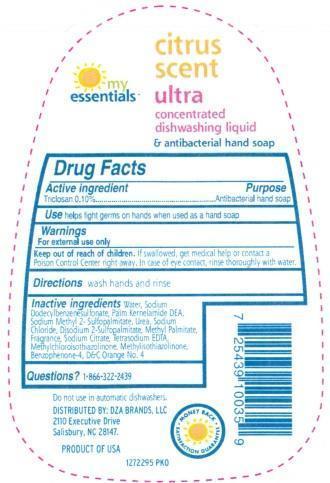 DRUG LABEL: My Essentials Citrus Scent
                
NDC: 63691-022 | Form: SOAP
Manufacturer: Sun Products Corporation
Category: otc | Type: HUMAN OTC DRUG LABEL
Date: 20141230

ACTIVE INGREDIENTS: TRICLOSAN 0.1 g/100 mL
INACTIVE INGREDIENTS: WATER; SODIUM DODECYLBENZENESULFONATE; SODIUM PALM KERNELATE; UREA; SODIUM CHLORIDE; DISODIUM 2-SULFOPALMITATE; METHYL PALMITATE; SODIUM CITRATE; EDETATE SODIUM; METHYLCHLOROISOTHIAZOLINONE; METHYLISOTHIAZOLINONE; SULISOBENZONE; D&C ORANGE NO. 4

Active ingredient

Triclosan 0.10%

INDICATIONS AND USAGE

Use helps fight germs on hands when used as a hand soap

WARNINGS

For external use only

Keep out of reach of children. If swallowed, get medical help or contact a Poison Control Center right away. In case of eye contact, rinse thoroughly with water.

DOSAGE AND ADMINISTRATION

Directions wash hands and rinse

PURPOSE

Antibacterial hand soap

INACTIVE INGREDIENT

Inactive ingredients Water, Sodium Dodecylbenzenesulfonate, Palm Kernelamide DEA, Sodium Methyl 2-Sulfopalmitate, Urea, Sodium Chloride, Disodium 2-Sulfopalmitate, Methyl Palmitate, Fragrance, Sodium Citrate, Tetrasodium EDTA, Methylchloroisothiazolinone, Methylisothiazolinone, Benzophenone-4, D&C Orange No. 4

Questions? 1-866-322-2439

PACKAGE LABEL

LBLFR

LBLBK